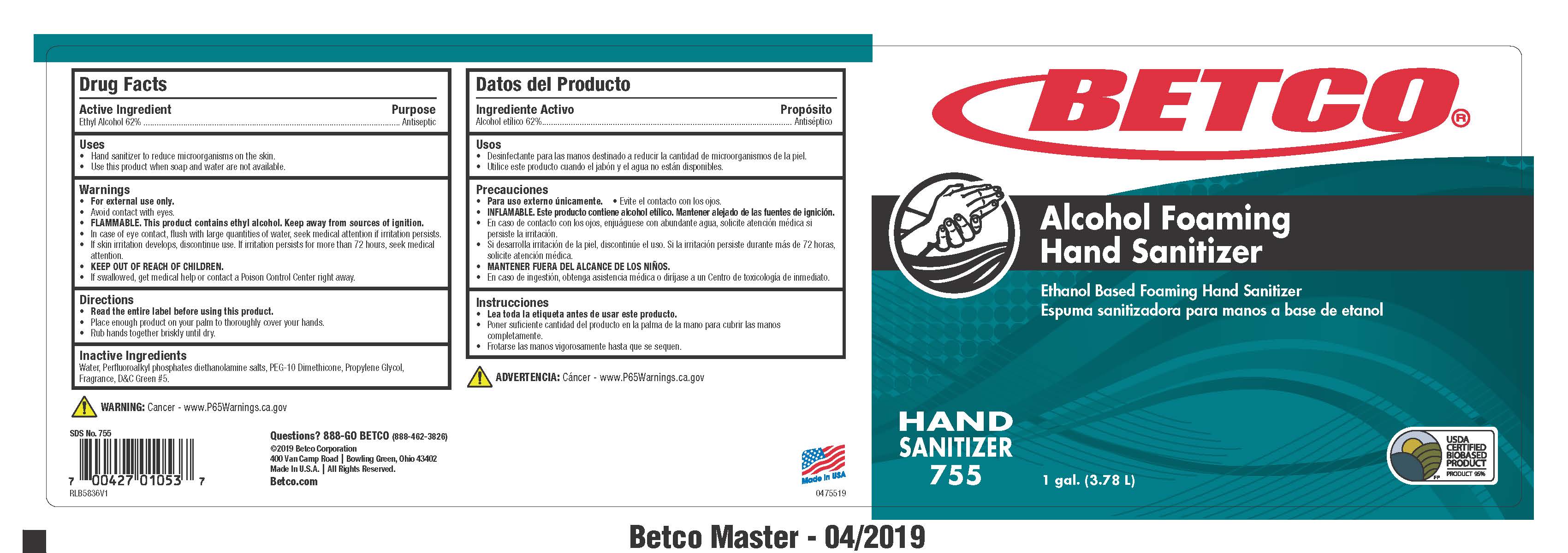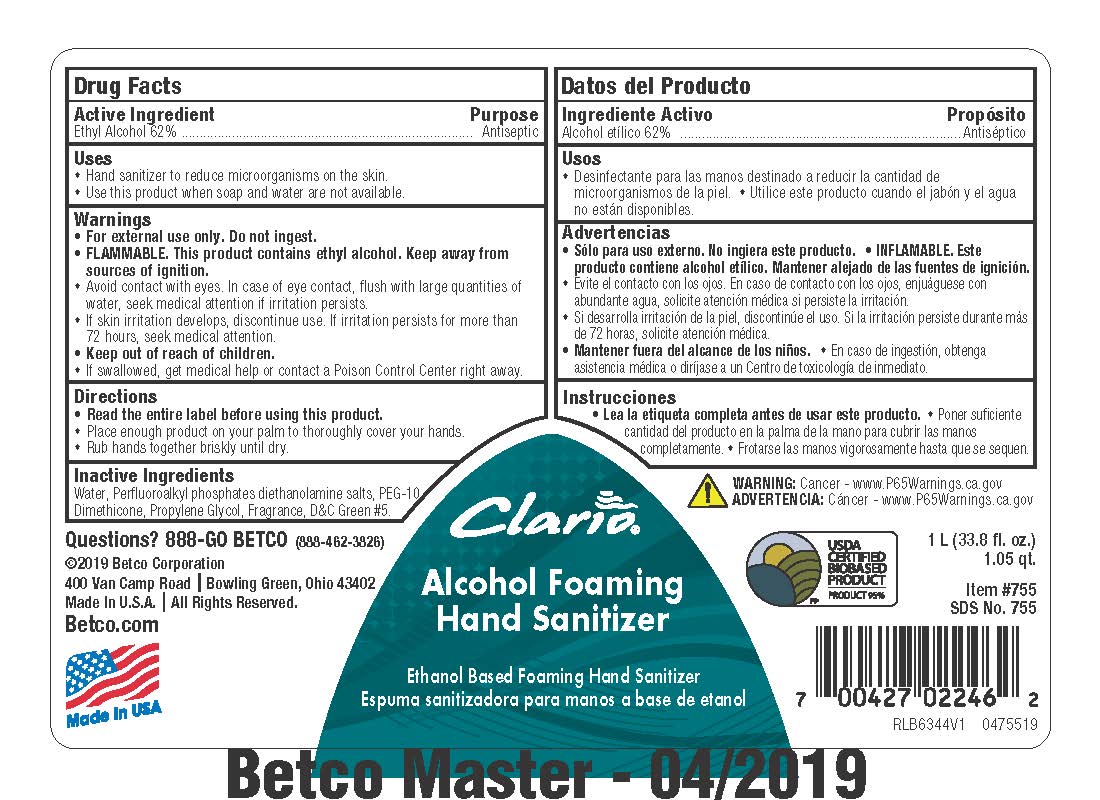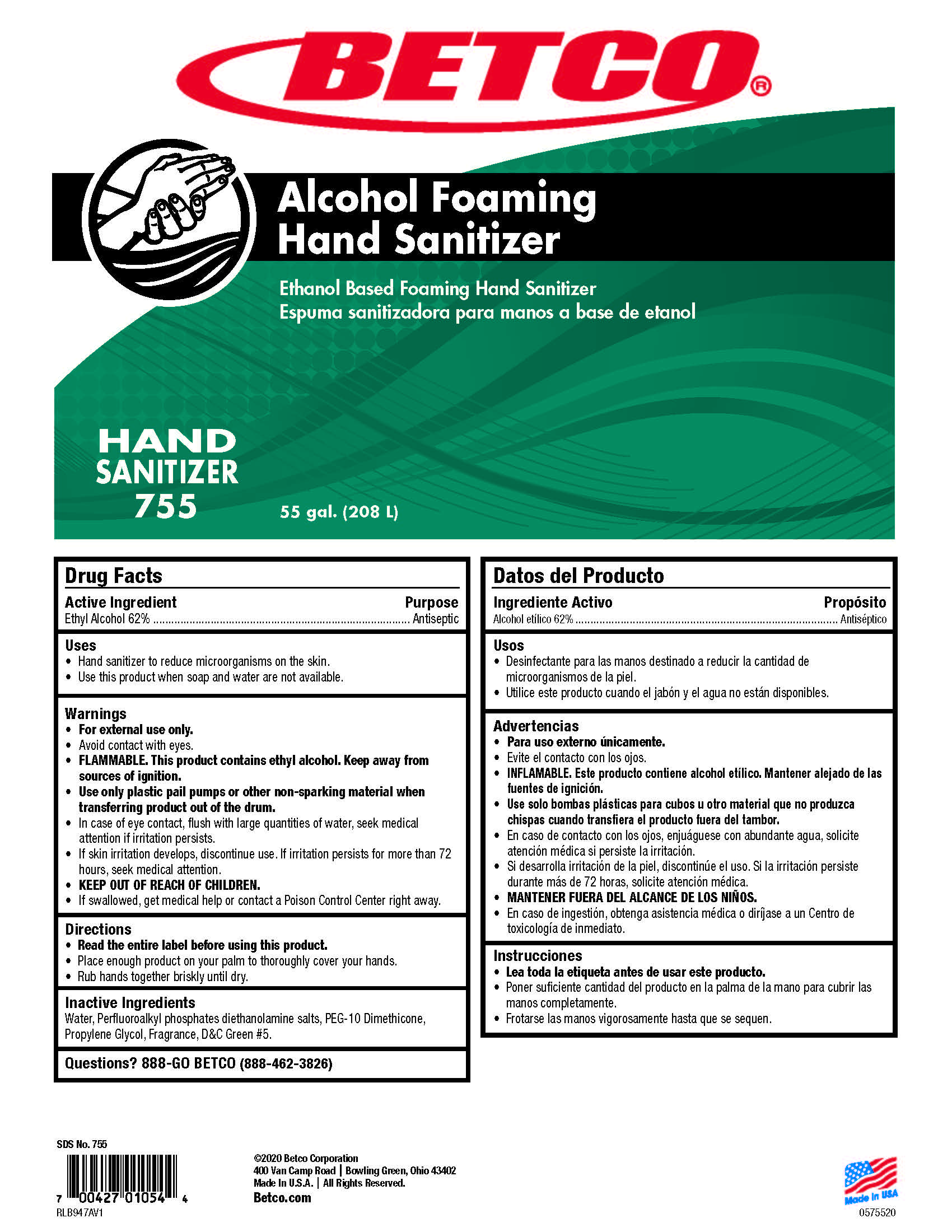 DRUG LABEL: Alcohol Foaming Hand Sanitizer
NDC: 65601-701 | Form: SOAP
Manufacturer: Betco Corporation, Ltd.
Category: otc | Type: HUMAN OTC DRUG LABEL
Date: 20210210

ACTIVE INGREDIENTS: ALCOHOL 0.62 mL/1 mL
INACTIVE INGREDIENTS: GERANIOL; DIETHANOLAMINE BIS(C8-C18 PERFLUOROALKYLETHYL)PHOSPHATE; BUTYLPHENYL METHYLPROPIONAL; HEXYL SALICYLATE; DIHYDROMYRCENOL; METHYL DIHYDROJASMONATE (SYNTHETIC); CYCLOMETHICONE 4; BIS-PEG-12 DIMETHICONE (70 MPA.S); DIETHANOLAMINE; HEXAMETHYLINDANOPYRAN; LINALOOL, (+/-)-; LEMON OIL; WATER; PROPYLENE GLYCOL; .BETA.-CITRONELLOL, (+/-)-; D&C GREEN NO. 5; ORANGE OIL; LIME OIL; GRAPEFRUIT OIL; MYRCENE

Alcohol Foaming Hand Sanitizer

Active Ingredient

Ethyl Alcohol 62%

Uses

- Use hand sanitizer to reduce microorganisms on the skin.
- Use this product when soap and water are not available.

Warnings

- For external use only. Do not ingest.
- FLAMMABLE. This product contains ethyl alcohol. Keep away from sources of ignition.
- Avoid contact with eyes. In case of eye contact, flush with large quantities of water, seek medical attention if irritation persists.
- If skin irritation develops, discontinue use. If irritation persists for more than 72 hours, seek medical attention.
- Keep out of reach of children.
- If swallowed, get medical help or contact a Poison Control Center right away.

Directions

- Read the entire label before using this product.
- Dispense 2 pumps of product onto palm of hand and rub thoroughly over all surfaces of both hands until dry.

Inactive Ingredients

Water, Propylene Glycol, Acrylic Polymer, Alkyl Phosphate Salts, Fragrance, DC Green #5.

Purpose

Antiseptic

Alcohol Foaming Hand Sanitizer

KEEP OUT OF REACH OF CHILDREN